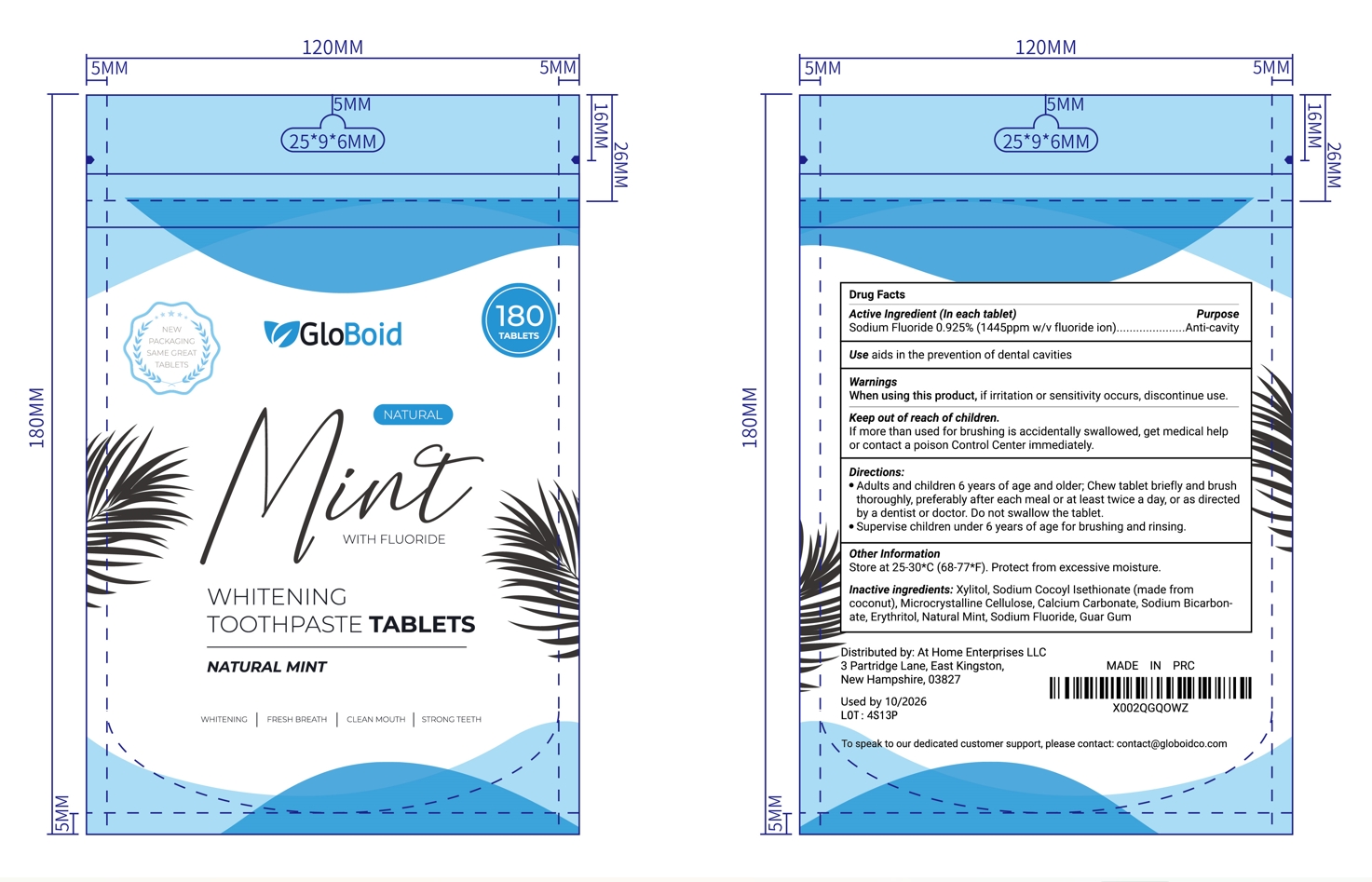 DRUG LABEL: Tooth
NDC: 83861-003 | Form: TABLET
Manufacturer: Henan Dailygreen Biotechnology Co. LTD
Category: otc | Type: HUMAN OTC DRUG LABEL
Date: 20241119

ACTIVE INGREDIENTS: SODIUM FLUORIDE 0.925 mg/100 1
INACTIVE INGREDIENTS: SODIUM COCOYL ISETHIONATE; GUAR GUM; CALCIUM CARBONATE; MINT; XYLITOL; SODIUM BICARBONATE; MICROCRYSTALLINE CELLULOSE; ERYTHRITOL

83861-003

Active ingredient

Sodium Fluoride 0.925% (1445ppm w/v fluoride ion)

Purpose

Anti-cavity

Use

aids in the prevention of dental cavities

Warnings

When using this product, if irritation or sensitivity occurs, discontinue use.

DO NOT USE

N/A

When using this product, if irritation or sensitivity occurs, discontinue use.

STOP USE

n/a

Keep out of reach of children.

If more than used for brushing is accidentally swallowed, get medical help or contact a poison Control Center immediately.

Directions

• Adults and children 6 years of age and older; Chew tablet briefly and brush thoroughly, preferably after each meal or at least twice a day, or as directed by a dentist or doctor. Do not swallow the tablet.

• Supervise children under 6 years of age for brushing and rinsing.

Other Information

Store at 25-30*C (68-77*F). Protect from excessive moisture.

Inactive ingredients

Xylitol, Sodium Cocoyl Isethionate (made from coconut), Microcrystalline Cellulose, Calcium Carbonate, Sodium Bicarbonate, Erythritol, Natural Mint, Sodium Fluoride, Guar Gum